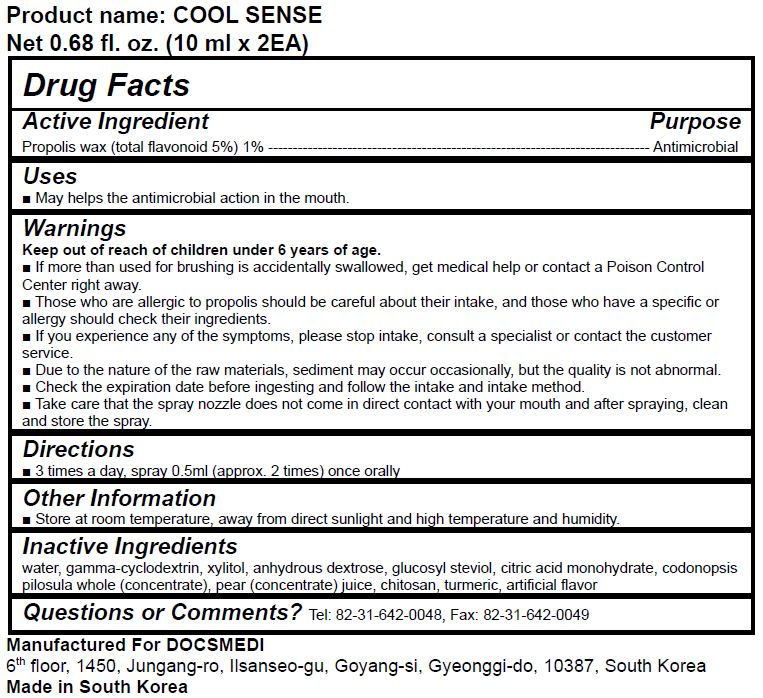 DRUG LABEL: COOL SENSE
NDC: 73706-0001 | Form: LIQUID
Manufacturer: Bncare Agriculture Co., Ltd.
Category: otc | Type: HUMAN OTC DRUG LABEL
Date: 20200319

ACTIVE INGREDIENTS: PROPOLIS WAX 1 g/100 mL
INACTIVE INGREDIENTS: WATER

ACTIVE INGREDIENT

Propolis extract (total flavonoid 5%)

PURPOSE

Can help the antimicrobial action in the mouth

Keep out of reach of children

INDICATIONS AND USAGE

3 times a day, spray 0.5ml (approx. 2 times) once orally

WARNINGS

1. Those who are allergic to propolis should be careful about their intake, and those who have a specific or allergy should check their ingredients.
2. If you experience any of the symptoms, please stop intake, consult a specialist or contact the customer service.
3. Due to the nature of the raw materials, sediment may occur occasionally, but the quality is not abnormal.
4. Check the expiration date before ingesting and follow the intake and intake method.
5. Take care that the spray nozzle does not come in direct contact with your mouth and after spraying, clean and store the spray.

INACTIVE INGREDIENT

water, gamma-cyclodextrin, xylitol, anhydrous dextrose, glucosyl steviol, citric acid monohydrate, codonopsis pilosula whole (concentrate), pear (concentrate) juice, chitosan, turmeric, artificial flavor

DOSAGE AND ADMINISTRATION

For dental use only